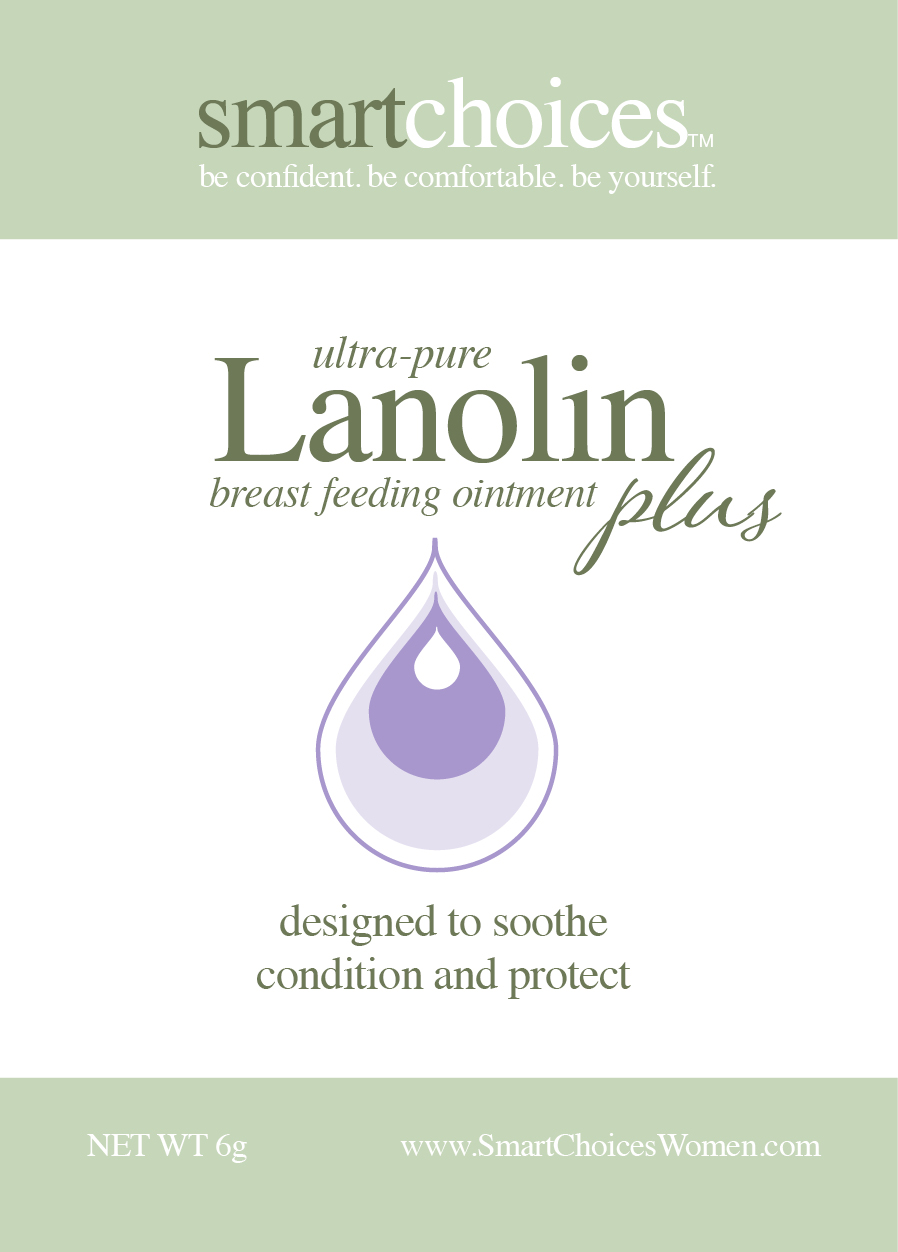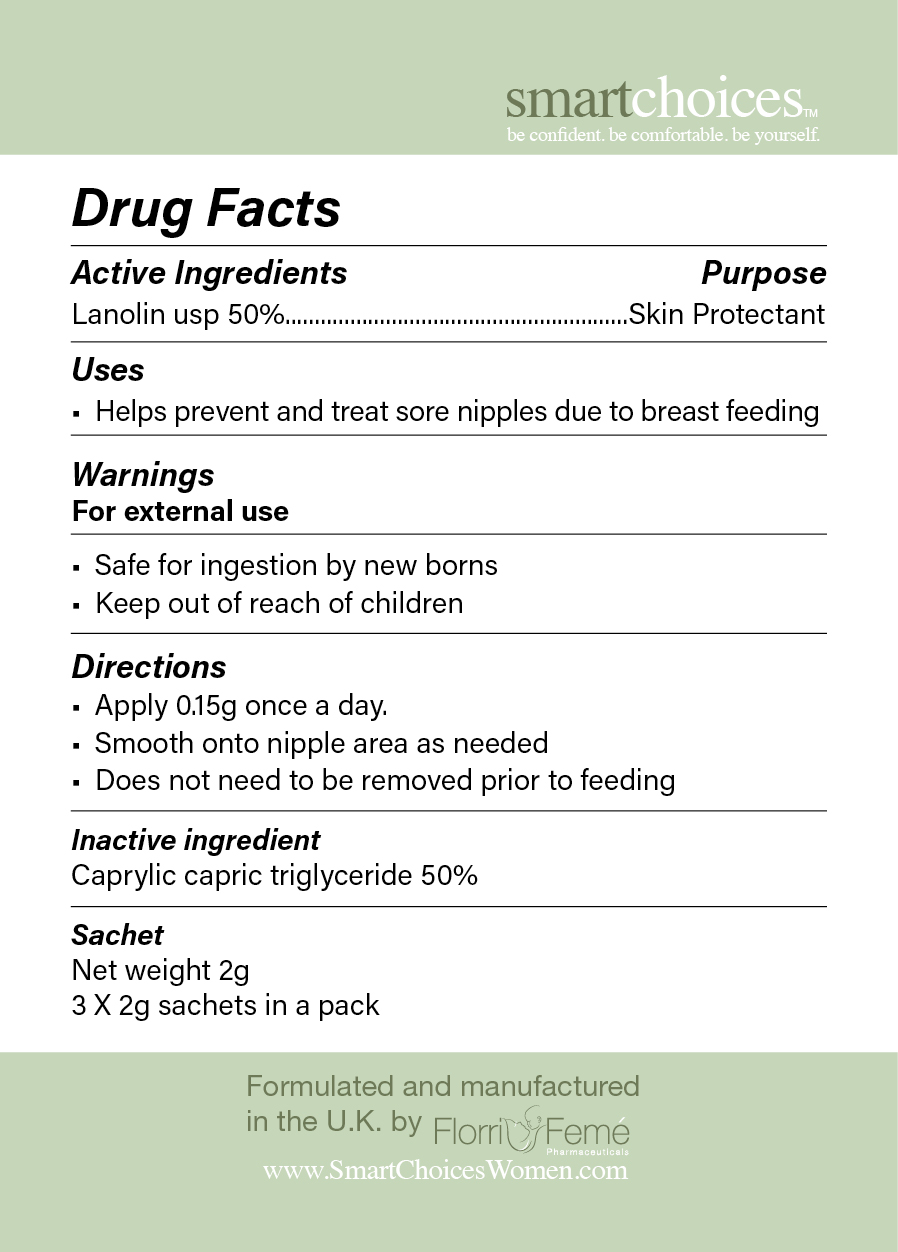 DRUG LABEL: Smartchoices Lanolin Plus
NDC: 70196-1333 | Form: CREAM
Manufacturer: Florri Feme Pharmaceuticals Ltd
Category: otc | Type: HUMAN OTC DRUG LABEL
Date: 20151023

ACTIVE INGREDIENTS: LANOLIN 1 mg/50 mg
INACTIVE INGREDIENTS: MEDIUM-CHAIN TRIGLYCERIDES

Directions

Apply 0.15g once a day.

Smooth onto nipple area as needed

For external use

Inactive Ingredient

Caprylic capric triglyceride 50%

USEAGE

Helps prevent and treat sore nipples due to breast feeding

Purpose

Helps prevent and treat sore nipples due to breast feeding

Warning

Keep out of reach of children

Active Ingredient

Lanolin usp 50%

Ultra pure Lanolin

Kamolan, Lanolin (ultra pure pharmacetical grade, USP modified Lanolin) Caprylic Capric Triglyceride (fractioned coconut oil)